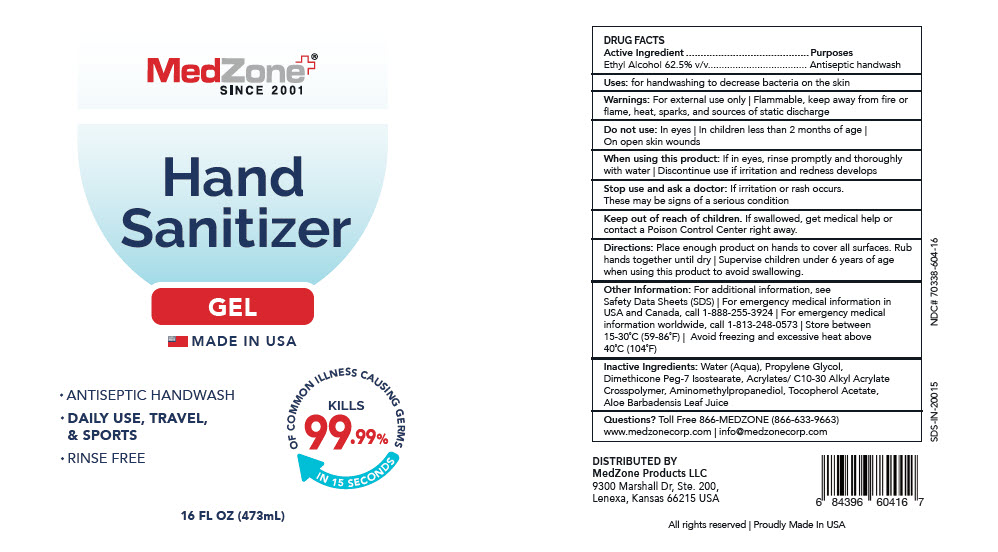 DRUG LABEL: Hand Sanitizer
NDC: 70338-604 | Form: GEL
Manufacturer: MedZone Products, LLC
Category: otc | Type: HUMAN OTC DRUG LABEL
Date: 20200326

ACTIVE INGREDIENTS: Alcohol 0.625 mL/1 mL
INACTIVE INGREDIENTS: Water; Propylene Glycol; Dimethicone Peg-7 Isostearate; Aminomethyl propanediol; .ALPHA.-TOCOPHEROL ACETATE; ALOE VERA LEAF

Hand Sanitizer

DRUG FACTS

Active Ingredient

Ethyl Alcohol 62.5% v/v

Purposes

Antiseptic handwash

Uses

for handwashing to decrease bacteria on the skin

Warnings

For external use only | Flammable, keep away from fire or flame, heat, sparks, and sources of static discharge

Do not use

In eyes | In children less than 2 months of age | On open skin wounds

When using this product

If in eyes, rinse promptly and thoroughly with water | Discontinue use if irritation and redness develops

Stop use and ask a doctor

If irritation or rash occurs. These may be signs of a serious condition

Keep out of reach of children. If swallowed, get medical help or contact a Poison Control Center right away.

Directions

Place enough product on hands to cover all surfaces. Rub hands together until dry | Supervise children under 6 years of age when using this product to avoid swallowing.

Other Information

For additional information, see Safety Data Sheets (SDS) | For emergency medical information in USA and Canada, call 1-888-255-3924 | For emergency medical information worldwide, call 1-813-248-0573 | Store between 15-30°C (59-86°F) | Avoid freezing and excessive heat above 40°C (104°F)

Inactive Ingredients

Water (Aqua), Propylene Glycol, Dimethicone Peg-7 Isostearate, Acrylates/ C10-30 Alkyl Acrylate Crosspolymer, Aminomethylpropanediol, Tocopherol Acetate, Aloe Barbadensis Leaf Juice

Questions?

Toll Free 866-MEDZONE (866-633-9663) www.medzonecorp.com | info@medzonecorp.com

DISTRIBUTED BY
MedZone Products LLC
9300 Marshall Dr, Ste. 200,
Lenexa, Kansas 66215 USA

PRINCIPAL DISPLAY PANEL - 473 mL Bottle Label

MedZone®
SINCE 2001

Hand
Sanitizer

GEL

MADE IN USA

- ANTISEPTIC HANDWASH
- DAILY USE, TRAVEL,
  & SPORTS
- RINSE FREE

OF COMMON ILLNESS CAUSING GERMS
KILLS
99.99%
IN 15 SECONDS

16 FL OZ (473mL)